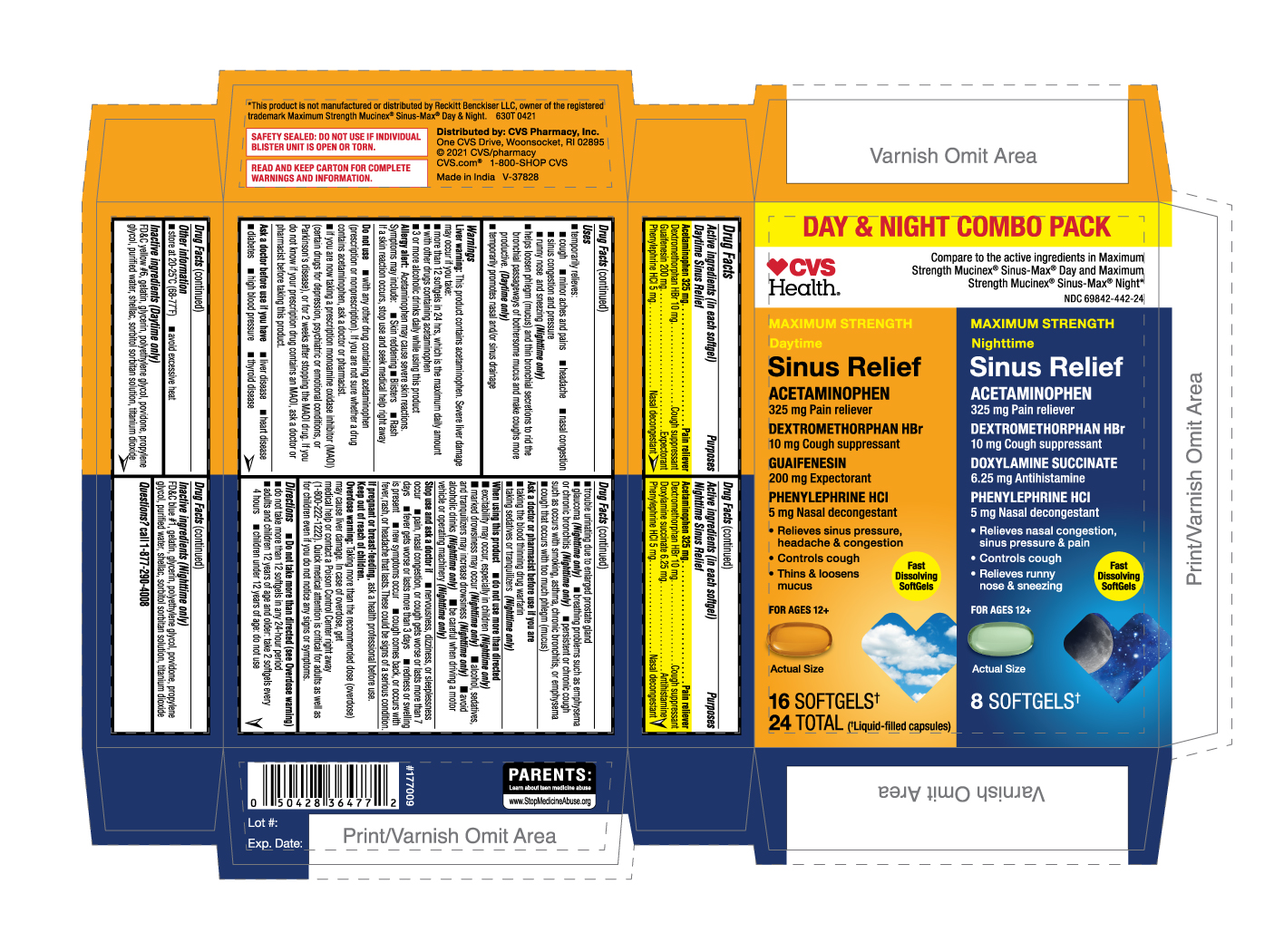 DRUG LABEL: MAXIMUM STRENGTH DAYTIME NIGHTTIME SINUS RELIEF
NDC: 69842-442 | Form: KIT | Route: ORAL
Manufacturer: CVS Pharmacy, Inc.
Category: otc | Type: HUMAN OTC DRUG LABEL
Date: 20250213

ACTIVE INGREDIENTS: DEXTROMETHORPHAN HYDROBROMIDE 10 mg/1 1; PHENYLEPHRINE HYDROCHLORIDE 5 mg/1 1; GUAIFENESIN 200 mg/1 1; ACETAMINOPHEN 325 mg/1 1; PHENYLEPHRINE HYDROCHLORIDE 5 mg/1 1; ACETAMINOPHEN 325 mg/1 1; DEXTROMETHORPHAN HYDROBROMIDE 10 mg/1 1; DOXYLAMINE SUCCINATE 6.25 mg/1 1
INACTIVE INGREDIENTS: GLYCERIN; POVIDONE; PROPYLENE GLYCOL; SHELLAC; SORBITOL; TITANIUM DIOXIDE; GELATIN; WATER; FD&C YELLOW NO. 6; POLYETHYLENE GLYCOL, UNSPECIFIED; SORBITOL; TITANIUM DIOXIDE; POVIDONE; WATER; SHELLAC; PROPYLENE GLYCOL; GLYCERIN; FD&C BLUE NO. 1; GELATIN; POLYETHYLENE GLYCOL, UNSPECIFIED

630T CVS 69842-442 MAXIMUM STRENGTH DAYTIME NIGHTTIME SINUS RELIEF

Active ingredients (in each softgel)
Daytime Sinus Relief
Acetaminophen 325 mg
Dextromethorphan HBr 10 mg
Guaifenesin 200 mg
Phenylephrine HCl 5 mg

Active ingredients (in each softgel)
Nighttime Sinus Relief
Acetaminophen 325 mg
Dextromethorphan HBr 10 mg
Doxylamine succinate 6.25 mg
Phenylephrine HCI 5 mg

Purposes
Daytime Sinus Relief
Pain reliever
Cough suppressant
Expectorant
Nasal decongestant

Purposes
Nighttime Sinus Relief
Pain reliever
Cough suppressant
Antihistamine
Nasal decongestant

Uses

- temporarily relieves:

cough

minor aches and pains

headache
nasal congestion
sinus congestion and pressure
runny nose and sneezing (Nighttime only)

- helps loosen phlegm (mucus) and thin bronchial secretions to rid the bronchial passageways of bothersome mucus and make coughs more productive. (Daytime only)
- temporarily promotes nasal and/or sinus drainage

WARNINGS
Liver warning:This product contains acetaminophen. Severe liver damage may occur if you take:

- more than 12 softgels in 24 hours, which is the maximum daily amount for this product
- with other drugs containing acetaminophen

Allergy alert: Acetaminophen may cause severe skin reactions. Symptoms may include:

- skin reddening
- Blisters
- Rash

If a skin reaction occurs, stop use and seek medical help right away.

Do not use

- with any other drug containing acetaminophen (prescription or nonprescription). If you are not sure whether a drug contains acetaminophen, ask a doctor or pharmacist.
- if you are now taking a prescription monoamine oxidase inhibitor (MAOI) (certain drugs for depression, psychiatric, or emotional conditions, or Parkinson's disease), or for 2 weeks after stopping the MAOI drug. If you do not know if your prescription drug contains an MAOI, ask a doctor or pharmacist before taking this product.

Ask a doctor before use if you have

- liver disease
- heart disease
- diabetes
- high blood pressure
- thyroid disease
- trouble urinating due to an enlarged prostate gland
- glaucoma (Nighttime only)
- breathing problems such as emphysema or chronic bronchitis (Nighttime only)
- persistent or chronic cough such as occurs with smoking, asthma, chronic bronchitis, or emphysema
- cough that occurs with too much phlegm (mucus)

Ask a doctor or pharmacist before use if you are

- taking the blood thinning drug warfarin
- taking sedatives or tranquilizers (Nighttime only)

When using this product

- do not use more than directed
- excitability may occur, especially in children (Nighttime only)
- marked drowsiness may occur (Nighttime only)
- alcohol, sedatives, and tranquilizers may increase drowsiness (Nighttime only)
- avoid alcoholic drinks (Nighttime only)
- be careful when driving a motor vehicle or operating machinery (Nighttime only)

PREGNANCY OR BREAST FEEDING

If pregnant or breast-feeding, ask a health professional before use.

Keep out of reach of children.
Overdose warning: Taking more than the recommended dose (overdose) may cause liver damage. In case of overdose, get medical help or contact a Poison Control Center right away (1-800-222-1222). Quick medical attention is critical for adults as well as for children even if you do not notice any signs or symptoms.

Directions

- do not take more than directed (see Overdose warning)
- do not take more than 12 softgels in any 24-hour period
- adults and children 12 years of age and older: take 2 softgels every 4 hours
- children under 12 years of age: do not use

OTHER INFORMATION

- store at 20-25°C (68-77°F)
- avoid excessive heat

Inactive ingredients (Daytime only)
FD&C yellow no. 6, gelatin, glycerin, polyethylene glycol, povidone, propylene glycol, shellac, sorbitol sorbitan solution, titanium dioxide, purified water.

Inactive ingredients (Nighttime only)
FD&C blue no. 1, gelatin, glycerin, polyethylene glycol, povidone, propylene glycol, shellac, sorbitol sorbitan solution, titanium dioxide, purified water

Questions? call 1-877-290-4008